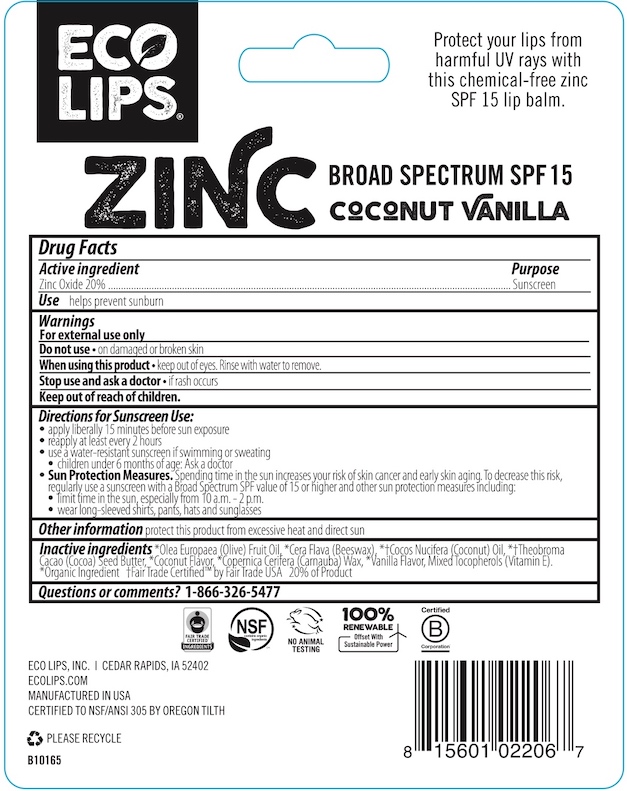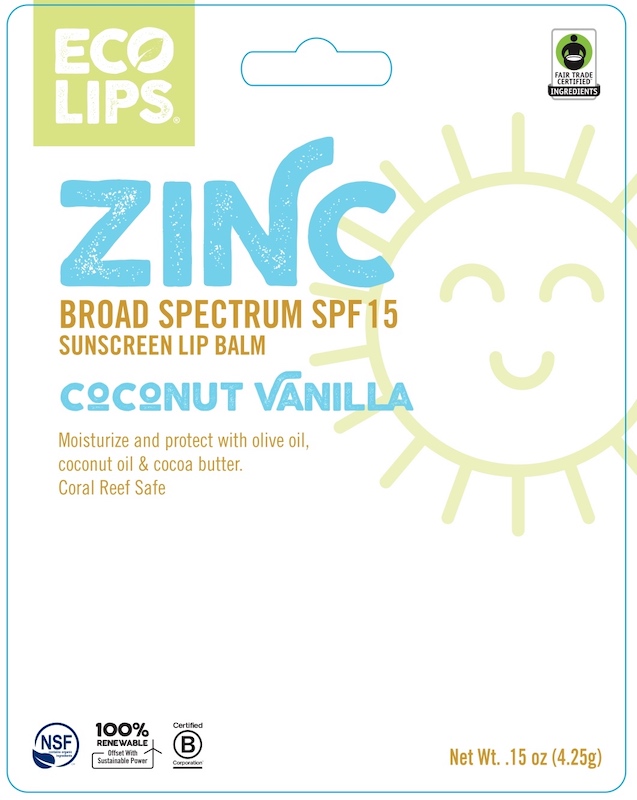 DRUG LABEL: Eco Lips Zinc Sunscreen Lip Balm
NDC: 75071-004 | Form: STICK
Manufacturer: Eco Lips. Inc.
Category: otc | Type: HUMAN OTC DRUG LABEL
Date: 20240417

ACTIVE INGREDIENTS: ZINC OXIDE 20 g/100 g
INACTIVE INGREDIENTS: CARNAUBA WAX; VANILLA; OLIVE OIL; YELLOW WAX; COCOA BUTTER; TOCOPHEROL; COCONUT OIL

206 Eco Lips Zinc Broad Spectrum SPF15

Drug Facts

Active ingredient

Zinc Oxide 20%

Purpose

Sunscreen

Use

helps prevent sunburn

Warnings

For external use only

Do not useon damaged or broken skin

WHEN USING

When using this productkeep out of eyes. Rinse with water to remove.

Stop use and ask a doctorif rash occurs

Keep out of reach of children.

DOSAGE AND ADMINISTRATION

Directions for Sunscreen Use:

- apply liberally 15 minutes before sun exposure
- reapply at least every 2 hours
- use a water-resistant sunscreen if swimming or sweating.
- children under 6 months of age: ask a doctor
- Sun Protection Measures.Spending time in the sun increases your risk of skin cancer and early skin aging. To decrease this risk
- limit time in the sun, especially from 10 a.m. - 2 p.m.
- wear long-sleeved shirts, pants, hats and sunglasses

Other information

protect this product from excessive heat and direct sun

Inactive ingredients

*Olea Europaea (Olive) Fruit Oil, *Cera Flava (Beeswax), *†Cocos Nucifera (Coconut) Oil, *†Theobroma Cacao (Cocoa) Seed Butter, *Coconut Flavor, *Copernical Cerifera (Carnauba) Wax, *Vanilla Flavor, Mixed Tocopherols (Vitamin E).

*Organic Ingredient † Fair Trade Certified™ by Fair Trade USA 20% of Product

Questions or comments?

1-866-326-5477

ECO LIPS, INC. | CEDAR RAPIDS, IA 52402

ECOLIPS.COM

MANUFACTURED IN USA

CERTIFIED TO NSF/ANSI 305 BY OREGON TILTH

PACKAGE LABEL

ECO LIPS®

ZINC

BROAD SPECTRUM SPF 15

SUNSCREEN LIP BALM

COCONUT VANILLA

Moisturize and protect with olive oil, coconut oil & cocoa butter.

Coral Reef Safe

Net Wt. .15 oz (4.25g)